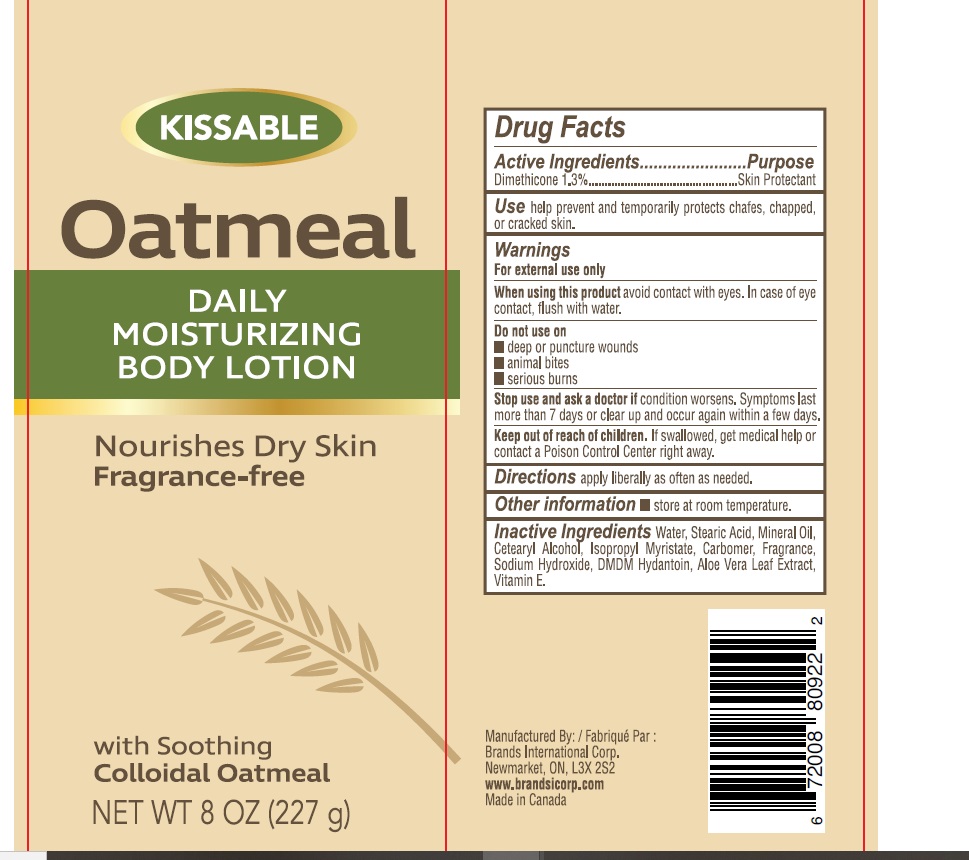 DRUG LABEL: Oatmeal Daily Moisturizing 8oz.
NDC: 50157-612 | Form: LOTION
Manufacturer: BRANDS INTERNATIONAL
Category: otc | Type: HUMAN OTC DRUG LABEL
Date: 20230222

ACTIVE INGREDIENTS: DIMETHICONE 3 g/227 g
INACTIVE INGREDIENTS: VITAMIN E POLYETHYLENE GLYCOL SUCCINATE; WATER; .BETA.-ELEOSTEARIC ACID; MINERAL OIL; GLYCERYL MONOSTEARATE; ISOPROPYL MYRISTATE; CARBOMER 1342; SODIUM HYDROXIDE; PROPYLPARABEN; STEARYL ALCOHOL; ALOE VERA LEAF; CETYL ALCOHOL; DMDM HYDANTOIN; EDETATE DISODIUM ANHYDROUS

KISSABLE - Oatmeal daily moisturizing lotion (8 oz.)

Active Ingredient Purpose

Dimethicone 1.3% ......... Skin Protectant

PURPOSE

Skin protectant

Keep out of reach of children. If swallowed, get medical help or contact a Poison Control Center immediately.

Uses

- Temporarily protects chafed, chapped or cracked skin

Warnings For external use only.

When using this product avoid contact with eyes. In case of eye contact, flush with water.

Stop use and ask a doctor if condition worsens. Symptoms last more than 7 days or clear up and occur again within a few days.

Do not use on

- Deep or puncture wounds
- Animal bites
- Serious burns

DOSAGE AND ADMINISTRATION

Directions apply liberally as often as needed.

Other Information store at room temperature.

Inactive Ingredients

Water, Isopropyl Myristate, Glycerin, Cetyl Alcohol, Mineral Oil, Fragrance, DMDM Hydantoin, Stearyl Alcohol, Carbomer, Sodium Hydroxide, Aloe Vera Leaf, Vitamin E, Isopropyl Myristate.